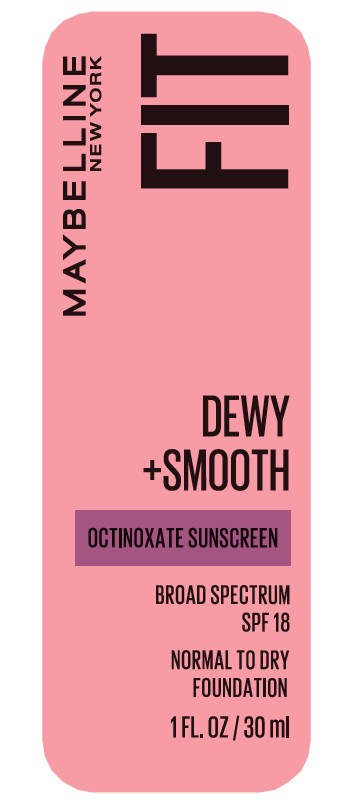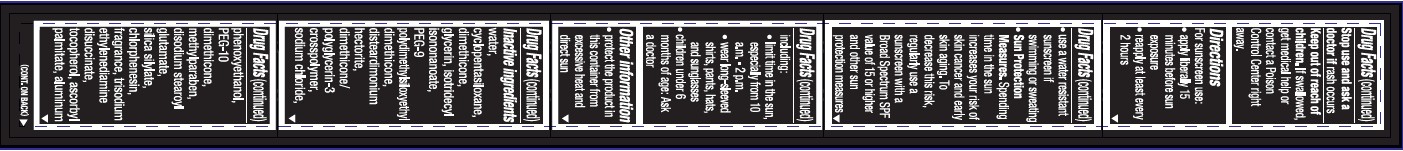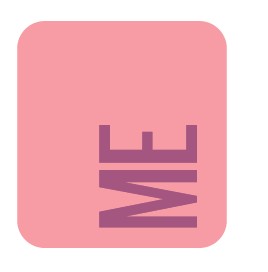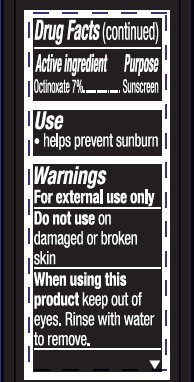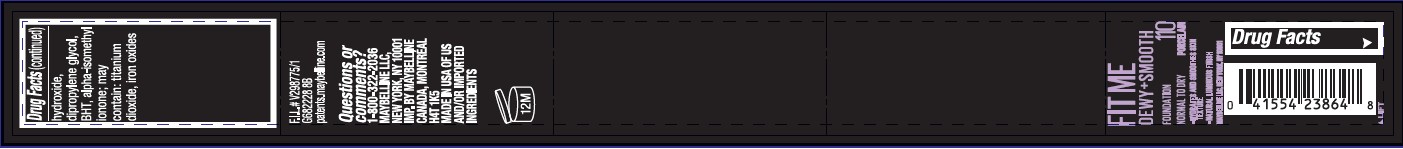 DRUG LABEL: Maybelline New York Fit Dewy Plus Smooth Normal to Dry Broad Spectrum SPF 18 Sunscreen
NDC: 82046-648 | Form: LOTION
Manufacturer: L'Oreal USA Products Inc
Category: otc | Type: HUMAN OTC DRUG LABEL
Date: 20231228

ACTIVE INGREDIENTS: OCTINOXATE 70 mg/1 mL
INACTIVE INGREDIENTS: WATER; CYCLOPENTASILOXANE; DIMETHICONE; GLYCERIN; ISOTRIDECYL ISONONANOATE; PEG-9 POLYDIMETHYLSILOXYETHYL DIMETHICONE; DISTEARDIMONIUM HECTORITE; DIMETHICONE/POLYGLYCERIN-3 CROSSPOLYMER; SODIUM CHLORIDE; PHENOXYETHANOL; PEG-10 DIMETHICONE (600 CST); METHYLPARABEN; DISODIUM STEAROYL GLUTAMATE; CHLORPHENESIN; TRISODIUM ETHYLENEDIAMINE DISUCCINATE; TOCOPHEROL; ASCORBYL PALMITATE; ALUMINUM HYDROXIDE; DIPROPYLENE GLYCOL; BHT; ALPHA-ISOMETHYL IONONE; TITANIUM DIOXIDE; FERROSOFERRIC OXIDE; FERRIC OXIDE RED; FERRIC OXIDE YELLOW

Drug Facts

Active ingredient

Octinoxate 7%

Purpose

Sunscreen

Use

- helps prevent sunburn

Warnings

For external use only

Do not use

on damaged or broken skin

When using this product

keep out of eyes. Rinse with water to remove.

Stop use and ask a doctor if

rash occurs

Keep out of reach of children.

If swallowed, get medical help or contact a Poison Control Center right away.

Directions

For sunscreen use:

● apply liberally 15 minutes before sun exposure

● reapply at least every 2 hours

● use a water resistant sunscreen if swimming or sweating

● children under 6 months of age: Ask a doctor

Spending time in the sun increases your risk of skin cancer and early skin aging. To decrease this risk, regularly use a sunscreen with a Broad Spectrum SPF value of 15 or higher and other sun protection measures including:

● limit time in the sun, especially from 10 a.m. – 2 p.m.

● wear long-sleeved shirts, pants, hats, and sunglasses

● children under 6 months of age: Ask a doctor

Other information

- protect the product in this container from excessive heat and direct sun

Inactive ingredients

water, cyclopentasiloxane, dimethicone, glycerin, isotridectyl isononanoate, PEG-9 polydimethylsiloxyethyl dimethicone, disteardimonium hectorite, dimethicone/polyglycerin-3 crosspolymer, sodium chloride, phenoxyethanol, PEG-10 dimethicone, methylparaben, disodium stearoyl glutamate, silica silylate, chlorphenesin, fragrance, trisodium ethylenediamine disuccinate, tocopherol, ascorbyl palmitate, aluminum hydroxide, dipropylene glycol, BHT, alpha-isomethyl ionone; may contain: titanium dioxide, iron oxides

Questions or comments?

1-800-322-2036